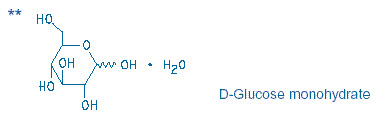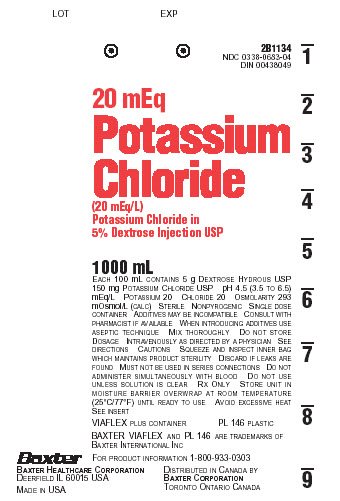 DRUG LABEL: Potassium Chloride in Dextrose
NDC: 0338-0683 | Form: INJECTION, SOLUTION
Manufacturer: Baxter Healthcare Company
Category: prescription | Type: HUMAN PRESCRIPTION DRUG LABEL
Date: 20190715

ACTIVE INGREDIENTS: POTASSIUM CHLORIDE 150 mg/100 mL; DEXTROSE MONOHYDRATE 5 g/100 mL
INACTIVE INGREDIENTS: WATER

HIGHLIGHTS OF PRESCRIBING INFORMATION

These highlights do not include all the information needed to use POTASSIUM CHLORIDE IN DEXTROSE INJECTION safely and effectively. See full prescribing information for POTASSIUM CHLORIDE IN DEXTROSE INJECTION.
POTASSIUM CHLORIDE IN DEXTROSE injection, for intravenous use
Initial U.S. Approval: 1979

RECENT MAJOR CHANGES

Contraindications (4) 07/2019

Warnings and Precautions (5.1, 5.2, 5.3, 5.4, 5.5, 5.6, 5.7) 07/2019

1 INDICATIONS AND USAGE

Potassium Chloride in Dextrose Injection is indicated as a source of water, electrolytes and calories. (1)

2 DOSAGE AND ADMINISTRATION

- Only for intravenous infusion. (2.1, 5.2)
- See full prescribing information for information on preparation, administration, dosing considerations and instructions for use. (2.1, 2.2,2.3)

3 DOSAGE FORMS AND STRENGTHS

Injection: 20 mEq Potassium Chloride in 5% Dextrose Injection, USP in a 1000 mL single-dose flexible container. (3)

4 CONTRAINDICATIONS

- Known hypersensitivity to potassium chloride or dextrose (4, 5.1)
- Clinically significant hyperkalemia (4, 5.2)
- Clinically significant hyperglycemia (4, 5.3)

5 WARNINGS AND PRECAUTIONS

- Hypersensitivity Reactions: monitor for signs and symptoms and discontinue infusion if reactions occur. (5.1)
- Hyperkalemia: May result in cardiac arrhythmias. Avoid use in patients with, or at risk for, hyperkalemia. If use cannot be avoided, use a product with a low amount of potassium chloride, infuse slowly and monitor serum potassium concentrations and ECGs. (5.2)
- Hyperglycemia or Hyperosmolar Hyperglycemic State: Monitor blood glucose and administer insulin as needed. (5.3, 8.4)
- Hyponatremia: Avoid in patients with or at risk for hyponatremia. If use cannot be avoided, monitor serum sodium concentrations. (5.4, 8.4)
- Hypokalemia: Avoid in patients with or at risk for hypokalemia. If use cannot be avoided, monitor serum potassium levels. (5.5)
- Fluid Overload: Avoid in patients with or at risk for fluid and/or solute overloading. If use cannot be avoided, monitor daily fluid balance and electrolyte, concentrations and acid-base balance, as needed and especially during prolonged use. (5.6)
- Refeeding Syndrome: Monitor severely undernourished patients and slowly increase nutrient intake. (5.7)

6 ADVERSE REACTIONS

Adverse reactions include electrolyte imbalances, hyperglycemia, and hypervolemia and injection site reactions. (6)

To report SUSPECTED ADVERSE REACTIONS, contact Baxter Healthcare at 1-866-888-2472 or FDA at 1-800-FDA-1088 or www.fda.gov/medwatch.

7 DRUG INTERACTIONS

- Other Products that Cause Hyperkalemia: Avoid use in patients receiving such products. If use cannot be avoided, monitor serum potassium concentrations. (7.1)
- Other Products that Affect Glycemic Control, Vasopressin or Fluid and/or Electrolyte Balance: Monitor blood glucose concentrations, fluid balance serum electrolyte concentrations and acid-base balance. (7.2)

FULL PRESCRIBING INFORMATION

1 INDICATIONS AND USAGE

Potassium Chloride in Dextrose Injection is indicated as a source of water, electrolytes and calories.

2 DOSAGE AND ADMINISTRATION

2.1 Important Administration Instructions

- Potassium Chloride in Dextrose Injection is only for intravenous infusion [see Warnings and Precautions (5.2)].
- For patients receiving Potassium Chloride in Dextrose Injection at greater than maintenance rates, frequent monitoring of serum potassium concentrations and serial electrocardiograms (ECGs) are recommended.
- The osmolarity of Potassium Chloride in Dextrose Injection is 293 mOsmol/L (calc). Peripheral administration is generally acceptable; however; consider central vein administration if there is peripheral vein irritation, phlebitis, and/or associated pain.
- Do not administer Potassium Chloride in Dextrose Injection simultaneously with blood products through the same administration set because of the possibility of pseudo agglutination or hemolysis.
- To prevent air embolism, use a non-vented infusion set or close the vent on a vented set, avoid multiple connections, do not connect flexible containers in series, fully evacuate residual gas in the container prior to administration, do not pressurize the flexible container to increase flow rates, and if administration is controlled by a pumping device, turn off pump before the container runs dry.
- Prior to infusion, visually inspect the solution for particulate matter. The solution should be clear and there should be no precipitates. Do not administer unless solution is clear and container is undamaged.
- Use of a final filter is recommended during administration of parenteral solutions, where possible.

2.2 Recommended Dosage

The infusion rate and volume depends on the age, weight, clinical and metabolic conditions of the patient and concomitant therapy. Electrolyte supplementation may be indicated according to the clinical needs of the patient.

The administration rate should be governed, especially for premature infants with low birth weight, during the first few days of therapy, by the patient’s tolerance to dextrose. Increase the infusion rate gradually as indicated by frequent monitoring of blood glucose concentrations [see Warnings and Precautions (5.1), Use in Specific Populations (8.4)].

2.3 Instructions for Use

To Open

- Do not remove container from overwrap until ready to use.
- Tear overwrap down side at slit and remove solution container.
- Visually inspect the container. Some opacity of the plastic due to moisture absorption during the sterilization process may be observed. This is normal and does not affect the solution quality or safety. The opacity will diminish gradually. Evaluate the following:
- If the outlet port protector is damaged, detached, or not present, discard container.
- Check to ensure the solution is clear and there are no precipitates. Discard if there is a color change and/or the appearance of precipitates, insoluble complexes or crystals.
- Check for minute leaks by squeezing inner bag firmly. If leaks are found, discard container.

Preparation for Administration

To Add Medication

- Additives may be incompatible. Complete information is not available. Do not use additives known or determined to be incompatible.
- Before adding a substance or medication, verify that it is soluble and/or stable in Potassium Chloride in Dextrose Injection and that the pH range of Potassium Chloride in Dextrose Injection is appropriate.
- Consult with pharmacist, if available. If, in the informed judgment of the healthcare provider, it is deemed advisable to introduce additives, use aseptic technique.
- When introducing additives, consult the instructions for use of the medication to be added and other relevant literature.

To Add Medication Before Solution Administration

1. Prepare medication site.
2. Using syringe with 19 to 22 gauge needle, puncture resealable medication port and inject.
3. Mix solution and medication thoroughly. For high density medication such as potassium chloride, squeeze ports while ports are upright and mix thoroughly.
4. After addition, check to ensure the solution is clear and there are no precipitates. Discard if there is a color change and/or the appearance of precipitates, insoluble complexes or crystals.

To Add Medication During Solution Administration

1. Close clamp on the set.
2. Prepare medication site.
3. Using syringe with 19 to 22 gauge needle, puncture resealable medication port and inject.
4. Remove container from IV pole and/or turn to an upright position.
5. Evacuate both ports by squeezing them while container is in the upright position.
6. Mix solution and medication thoroughly.
7. After addition, check to ensure the solution is clear and there are no precipitates. Discard if there is a color change and/or the appearance of precipitates, insoluble complexes or crystals, do not use.
8. Return container to in use position and continue administration.

Storage

- Use promptly; do not store solutions containing additives.
- Single-dose container.
- Discard any unused portion.

3 DOSAGE FORMS AND STRENGTHS

Potassium Chloride in Dextrose Injection, USP is a clear solution of 20 mEq Potassium Chloride and 5% Dextrose in a 1000 mL single-dose, flexible container.

4 CONTRAINDICATIONS

Potassium Chloride in Dextrose Injection is contraindicated in patients with:

- known hypersensitivity to potassium chloride and/or dextrose [see Warnings and Precautions 5.1)]
- clinically significant hyperkalemia [see Warnings and Precautions (5.2)]
- clinically significant hyperglycemia [see Warnings and Precautions (5.3)]

5 WARNINGS AND PRECAUTIONS

5.1 Hypersensitivity Reactions

Hypersensitivity and infusion reactions, including anaphylaxis, have been reported with Potassium Chloride in Dextrose Injection [see Adverse Reactions (6)]. Stop the infusion immediately if signs or symptoms of a hypersensitivity or infusion reaction develops [see Contraindications (4)]. Appropriate therapeutic countermeasures must be instituted as clinically indicated.

5.2 Hyperkalemia

Potassium-containing solutions, including Potassium Chloride in Dextrose Injection may increase the risk of hyperkalemia. Hyperkalemia can be asymptomatic and manifest only by increased serum potassium concentrations and/or characteristic electrocardiographic (ECG) changes. Cardiac arrhythmias, some fatal, can develop at any time during hyperkalemia.

To avoid life threatening hyperkalemia, do not administer Potassium Chloride in Dextrose Injection as an intravenous push (i.e., intravenous injection manually with a syringe connected to the intravenous access, without quantitative infusion device [see Dosage and Administration (2.1)].

Patients at increased risk of developing hyperkalemia and cardiac arrhythmias include those:

- with severe renal impairment, acute dehydration, extensive tissue injury or burns, and certain cardiac disorders such as congestive heart failure or AV block (especially if they receive digoxin).
- with hyperosmolality, acidosis, or undergoing correction of alkalosis (conditions associated with a shift of potassium from intracellular to extracellular space).
- treated concurrently or recently with agents or products that can cause or increase the risk of hyperkalemia [see Drug Interactions (7.1)].

Avoid use of Potassium Chloride in Dextrose Injection in patients with, or at risk for, hyperkalemia. If use cannot be avoided, use a product with a low amount of potassium chloride, infuse slowly and monitor serum potassium concentrations and ECGs.

5.3 Hyperglycemia and Hyperosmolar Hyperglycemic State

The use of dextrose infusions in patients with impaired glucose tolerance may worsen hyperglycemia. Administration of dextrose at a rate exceeding the patient’s utilization rate may lead to hyperglycemia, coma, and death.

Hyperglycemia is associated with an increase in serum osmolality, resulting in osmotic diuresis, dehydration and electrolyte losses [see Warnings and Precautions (5.6)]. Patients with underlying central nervous system disease and renal impairment who receive dextrose infusions, may be at greater risk of developing hyperosmolar hyperglycemic state.

Monitor blood glucose concentrations and treat hyperglycemia to maintain concentrations within normal limits while administering Potassium Chloride in Dextrose Injection. Insulin may be administered or adjusted to maintain optimal blood glucose concentrations.

5.4 Hyponatremia

Potassium Chloride in Dextrose Injection is an isotonic solution [see Description, Table 1 (11)]. In the body, however, glucose containing fluids can become extremely physiologically hypotonic due to rapid glucose metabolization. Monitoring of serum sodium is particularly important for hypotonic fluids.

Depending on the tonicity of the solution, the volume and rate of infusion, and depending on a patient’s underlying clinical condition and capability to metabolize glucose, intravenous administration of glucose can cause electrolyte disturbances, most importantly hypo- or hyperosmotic hyponatremia.

The risk for hyponatremia is increased, in pediatric patients, elderly patients, postoperative patients, those with psychogenic polydipsia and in patients treated with medications that increase the risk of hyponatremia (such as certain diuretic, antiepileptic and psychotropic medications). Close clinical monitoring may be warranted.

Acute hyponatremia can lead to acute hyponatremic encephalopathy characterized by headache, nausea, seizures, lethargy and vomiting. Patients with brain edema are at particular risk of severe, irreversible and life-threatening brain injury. Patients at increased risk for developing complications of hyponatremia, such as hyponatremic encephalopathy include pediatric patients; women, in particular, premenopausal women; patients with hypoxemia; and in patients with underlying central nervous system disease [see Use in Specific Populations (8.4, 8.5)].

Rapid correction of hyponatremia is potentially dangerous with risk of serious neurologic complications such as osmotic demyelination syndrome with risk of seizures and cerebral edema. To avoid complications, monitor serum sodium and chloride concentrations, fluid status, acid-base balance, and signs of neurologic complications.

High volume infusion must be used with close monitoring in patients with cardiac or pulmonary failure, and in patients with non-osmotic vasopressin release (including SIADH), due to the risk of hospital-acquired hyponatremia.

5.5 Hypokalemia

Infusion of Potassium Chloride in Dextrose Injection may result in hypokalemia, leading to arrhythmias, muscle weakness, paralysis, heart block, and rhabdomyolysis.

Hypokalemic periodic paralysis, metabolic alkalosis, increased gastrointestinal losses (e.g., diarrhea, vomiting), prolonged low potassium diet or primary hyperaldosteronism may increase the risk of hypokalemia. If use cannot be avoided, monitor serum potassium levels.

5.6 Fluid Overload

Depending on the volume and rate of infusion, the patient’s underlying clinical condition and capability to metabolize dextrose, intravenous administration of Potassium Chloride in Dextrose Injection can cause fluid and/or solute overloading resulting in dilution of serum electrolyte concentrations, overhydration, congested states or pulmonary edema.

Avoid Potassium Chloride in Dextrose Injection in patients with or at risk for fluid and/or solute overloading. If use cannot be avoided, monitor fluid balance, electrolyte concentrations, and acid-base balance as needed and especially during prolonged use.

5.7 Refeeding Syndrome

Refeeding severely undernourished patients may result in the refeeding syndrome that is characterized by the shift of potassium, phosphorus, and magnesium intracellularly as the patient becomes anabolic. Thiamine deficiency and fluid retention may also develop. To prevent these complications, monitor severely undernourished patients and slowly increasing nutrient intake.

6 ADVERSE REACTIONS

The following adverse reactions associated with the use of Potassium Chloride in Dextrose Injection were identified in post marketing reports. Because these reactions were reported voluntarily from a population of uncertain size, it is not always possible to reliably estimate their frequency or establish a causal relationship to drug exposure.

The following clinically significant adverse reactions are described elsewhere in the labeling:

- Hypersensitivity reactions: including anaphylaxis and chills [see Warnings and Precautions (5.1)].
- Hyperkalemia, including cardiac arrest, as a manifestation [see Warnings and Precautions (5.2)]
- Hyponatremia and hyponatremic encephalopathy [see Warnings and Precautions (5.4)]
- Hypokalemia [see Warnings and Precautions (5.5)]
- Hypervolemia [see Warnings and Precautions (5.6)]
- Injection site reactions: infection at the site of injection, venous thrombosis or phlebitis extending from the site of injection, extravasation, infusion site rash, infusion site pain, infusion site vesicles, infusion site pruritus, pyrexia and chills

7 DRUG INTERACTIONS

7.1 Other Products that Cause Hyperkalemia

Administration of Potassium Chloride in Dextrose Injection in patients treated concurrently or recently with other products that can cause hyperkalemia or increase the risk of hyperkalemia (e.g., potassium-sparing diuretics, angiotensin-converting enzyme inhibitors, angiotensin receptor blockers) increases the risk of severe and potentially fatal hyperkalemia, in particular in the presence of other risk factors for hyperkalemia [see Warnings and Precautions (5.2)]. Avoid use of Potassium Chloride in Dextrose Injection in patients receiving such products. If use cannot be avoided, monitor serum potassium concentrations.

7.2 Other Products that Affect Glycemic Control, Vasopressin or Fluid and/or Electrolyte Balance

Potassium Chloride in Dextrose Injection can affect glycemic control, vasopressin and fluid and/or electrolyte balance [see Warnings and Precautions (5.3, 5.4, 5.5, 5.6)]. Monitor blood glucose concentrations, fluid balance, serum electrolyte concentrations and acid-base balance when using Potassium Chloride in Dextrose Injection in patients treated with other substances that affect glycemic control, vasopressin or fluid and/or electrolyte balance.

8 USE IN SPECIFIC POPULATIONS

8.1 Pregnancy

Risk Summary

Appropriate administration of Potassium Chloride in Dextrose Injection during pregnancy is not expected to cause adverse developmental outcomes, including congenital malformations. Animal reproduction studies have not been conducted with Potassium Chloride in Dextrose Injection.

The estimated background risk of major birth defects and miscarriage for the indicated population is unknown. All pregnancies have a background risk of birth defect, loss, or other adverse outcomes. In the U.S. general population, the estimated background risk of major birth defects and miscarriage in clinically recognized pregnancies is 2 to 4% and 15 to 20%, respectively.

8.2 Lactation

Risk Summary

Potassium is present in human breast milk. There are no data on the effects of Potassium Chloride in Dextrose Injection on a breastfed infant or the effects on milk production.

The developmental and health benefits of breastfeeding should be considered along with the mother’s clinical need for Potassium Chloride in Dextrose Injection and any potential adverse effects on the breastfed infant from Potassium Chloride in Dextrose Injection or from the underlying maternal condition.

8.4 Pediatric Use

The safety profile of Potassium Chloride in Dextrose Injection in pediatric patients is similar to adults.

Neonates, especially premature infants with low birth weight, are at increased risk of developing hypo- or hyperglycemia and therefore need close monitoring during treatment with intravenous glucose solutions to ensure adequate glycemic control in order to avoid potential long term adverse effects.

Closely monitor plasma electrolyte concentrations in pediatric patients who may have impaired ability to regulate fluids and electrolytes. In very low birth weight infants, excessive or rapid administration of Potassium Chloride in Dextrose Injection may result in increased serum osmolality and risk of intracerebral hemorrhage.

Children (including neonates and older children) are at increased risk of developing hyponatremia as well as for developing hyponatremic encephalopathy.

8.5 Geriatric Use

Potassium Chloride in Dextrose Injection is known to be substantially excreted by the kidney, and the risk of adverse reactions to this product may be greater in patients with impaired renal function [see Warnings and Precautions (5.2, 5.3)].

Elderly patients are at increased risk of developing hyponatremia as well as for developing hyponatremic encephalopathy [see Warnings and Precautions (5.4)].

Dose selection for an elderly patient should be cautious, starting at the low end of the dosing range, reflecting the greater frequency of decreased hepatic, renal, or cardiac function, and of concomitant disease or other drug therapy.

8.6 Renal Impairment

Administration of Potassium Chloride in Dextrose Injection in patients with renal impairment may result in hyperkalemia, hyponatremia, and/or fluid overload. Monitor patients with renal impairment for development of these adverse reactions [see Warnings and Precautions (5.2, 5.4, 5.6)].

10 OVERDOSAGE

Excess administration of Potassium Chloride in Dextrose Injection can cause:

Hyperkalemia
2. Manifestations of hyperkalemia may include:
  - disturbances in cardiac conduction and arrhythmias, including bradycardia, heart block, asystole, ventricular tachycardia, ventricular fibrillation, and ECG changes (peaking of T waves, loss of P waves, and QRS widening)
  - hypotension,
  - muscle weakness up to and including muscular and respiratory paralysis, paresthesia of extremities,
  - gastrointestinal symptoms (ileus, nausea, vomiting, abdominal pain)
The presence of any ECG findings that are suspected to be caused by hyperkalemia should be considered a medical emergency.
If hyperkalemia is present or suspected, discontinue the infusion immediately and institute close ECG, laboratory and other monitoring and, as necessary, corrective therapy to reduce serum potassium concentrations [see Warnings and Precautions (5.2)].
Other Electrolyte and Fluid Disorders
6. Hyperglycemia, hyperosmolality, and adverse effects on water and electrolyte balance, and corresponding complications, which can be fatal [see Warnings and Precautions (5.3, 5.6)].
7. Hyponatremia, manifestations may include seizures, coma, cerebral edema and death) [see Warnings and Precautions (5.4)].
8. Fluid overload (which can lead to central and/or peripheral edema) [see Warnings and Precautions (5.6)].
9. Hypernatremia, especially in patients with severe renal impairment.

Interventions include discontinuation of the infusion, dose reduction, monitoring of fluid balance, electrolyte concentrations and acid-base balance and institution of appropriate corrective measures such as administration of exogenous insulin.

11 DESCRIPTION

Potassium Chloride in Dextrose Injection, USP is a sterile, nonpyrogenic solution for fluid and electrolyte replenishment and caloric supply in a single-dose container for intravenous administration. It contains no antimicrobial agents. Composition, osmolarity, pH, ionic concentration and caloric content are shown in Table 1.

Table 1 | Size (mL) | Composition (g/L) |  | [Normal physiologic osmolarity range is approximately 280 to 310 mOsmol/L.] Osmolarity (mOsmol/L) (calc.) | pH | Ionic Concentration (mEq/L) |  | Caloric Content (kcal/L)
Table 1 | Size (mL) | **Dextrose Hydrous, USP | Potassium Chloride, USP (KCl) | [Normal physiologic osmolarity range is approximately 280 to 310 mOsmol/L.] Osmolarity (mOsmol/L) (calc.) | pH | Potassium | Chloride | Caloric Content (kcal/L)
Potassium Chloride in 5% Dextrose Injection, USP | Size (mL) | **Dextrose Hydrous, USP | Potassium Chloride, USP (KCl) | [Normal physiologic osmolarity range is approximately 280 to 310 mOsmol/L.] Osmolarity (mOsmol/L) (calc.) | pH | Potassium | Chloride | Caloric Content (kcal/L)
mEq Potassium | Size (mL) | **Dextrose Hydrous, USP | Potassium Chloride, USP (KCl) | [Normal physiologic osmolarity range is approximately 280 to 310 mOsmol/L.] Osmolarity (mOsmol/L) (calc.) | pH | Potassium | Chloride | Caloric Content (kcal/L)
20 mEq | 1000 | 50 | 1.5 | 293 | 4.5 (3.5 to 6.5) | 20 | 20 | 170

Dextrose is derived from corn.

The VIAFLEX Plus plastic container is fabricated from a specially formulated polyvinyl chloride (PL 146 Plastic). VIAFLEX Plus on the container indicates the presence of a drug additive in a drug vehicle. The VIAFLEX Plus plastic container system utilizes the same container as the VIAFLEX plastic container system. The amount of water that can permeate from inside the container into the overwrap is insufficient to affect the solution significantly. Solutions in contact with the plastic container can leach out certain of its chemical components in very small amounts within the expiration period, e.g., di-2-ethylhexyl phthalate (DEHP), up to 5 parts per million. However, the safety of the plastic has been confirmed in tests in animals according to USP biological tests for plastic containers as well as by tissue culture toxicity studies.

12 CLINICAL PHARMACOLOGY

12.1 Mechanism of Action

Potassium Chloride in Dextrose Injection is a source of water, electrolytes and calories. It is capable of inducing diuresis depending on the clinical condition of the patient.

16 HOW SUPPLIED/STORAGE AND HANDLING

Potassium Chloride in 5% Dextrose Injection, is a clear solution in 1000 mL single-dose, flexible containers available as follows:

Code | Size (mL) | NDC | Product Name
2B1134 | 1000 | 0338-0683-04 | 20 mEq Potassium Chloride in 5% Dextrose Injection, USP

Storage: Avoid excessive heat. Store at room temperature (25°C); brief exposure up to 40°C does not adversely affect the product.

17 PATIENT COUNSELING INFORMATION

Inform patients, caregivers or home healthcare providers of the following risks of Potassium Chloride in Dextrose Injection:

- Hypersensitivity reactions [see Warnings and Precautions (5.1)]
- Hyperkalemia [see Warnings and Precautions (5.2)]
- Hyperglycemia and hyperosmolar hyperglycemic state [see Warnings and Precautions (5.3)]
- Hyponatremia [see Warnings and Precautions (5.4)]
- Hypokalemia [see Warnings and Precautions (5.5)]
- Fluid overload [see Warnings and Precautions (5.6)]
- Refeeding syndrome [see Warnings and Precautions (5.7)]

Baxter Healthcare Corporation
Deerfield, IL 60015 USA
Printed in USA

Distributed in Canada by
Baxter Corporation
Mississauga, ON L5N 0C2

07-19-75-361

Baxter and Viaflex are trademarks of Baxter International Inc.

PACKAGE/LABEL PRINCIPAL DISPLAY PANEL

Container Label

Container Label

2B1134
NDC 0338-0683-04
DIN 00438049

20 mEq
Potassium Chloride
(20 mEq/L)
Potassium Chloride in
5% Dextrose Injection USP

1000 mL

EACH 100 mL CONTAINS 5 g DEXTROSE HYDROUS USP
150 mg POTASSIUM CHLORIDE USP pH 4.5 (3.5 TO 6.5)
mEq/L POTASSIUM 20 CHLORIDE 20 OSMOLARITY 293
mOsmol/L (CALC) STERILE NONPYROGENIC SINGLE DOSE
CONTAINER ADDITIVES MAY BE INCOMPATIBLE CONSULT WITH
PHARMACIST IF AVAILABLE WHEN INTRODUCING ADDITIVES USE
ASEPTIC TECHNIQUE MIX THOROUGHLY DO NOT STORE
DOSAGE INTRAVENOUSLY AS DIRECTED BY A PHYSICIAN SEE
DIRECTIONS CAUTIONS SQUEEZE AND INSPECT INNER BAG
WHICH MAINTAINS PRODUCT STERILITY DISCARD IF LEAKS ARE
FOUND MUST NOT BE USED IN SERIES CONNECTIONS DO NOT
ADMINISTER SIMULTANEOUSLY WITH BLOOD DO NOT USE
UNLESS SOLUTION IS CLEAR RX ONLY STORE UNIT IN
MOISTURE BARRIER OVERWRAP AT ROOM TEMPERATURE
(25°C/77°F) UNTIL READY TO USE AVOID EXCESSIVE HEAT
SEE INSERT
VIAFLEX PLUS CONTAINER PL 146 PLASTIC
BAXTER VIAFLEX AND PL 146 ARE TRADEMARKS OF
BAXTER INTERNATIONAL INC
FOR PRODUCT INFORMATION 1-800-933-0303

Baxter Logo

BAXTER HEALTHCARE CORPORATION
DEERFIELD IL 60015 USA

MADE IN USA

DISTRIBUTED IN CANADA BY
BAXTER CORPORATION
TORONTO ONTARIO CANADA